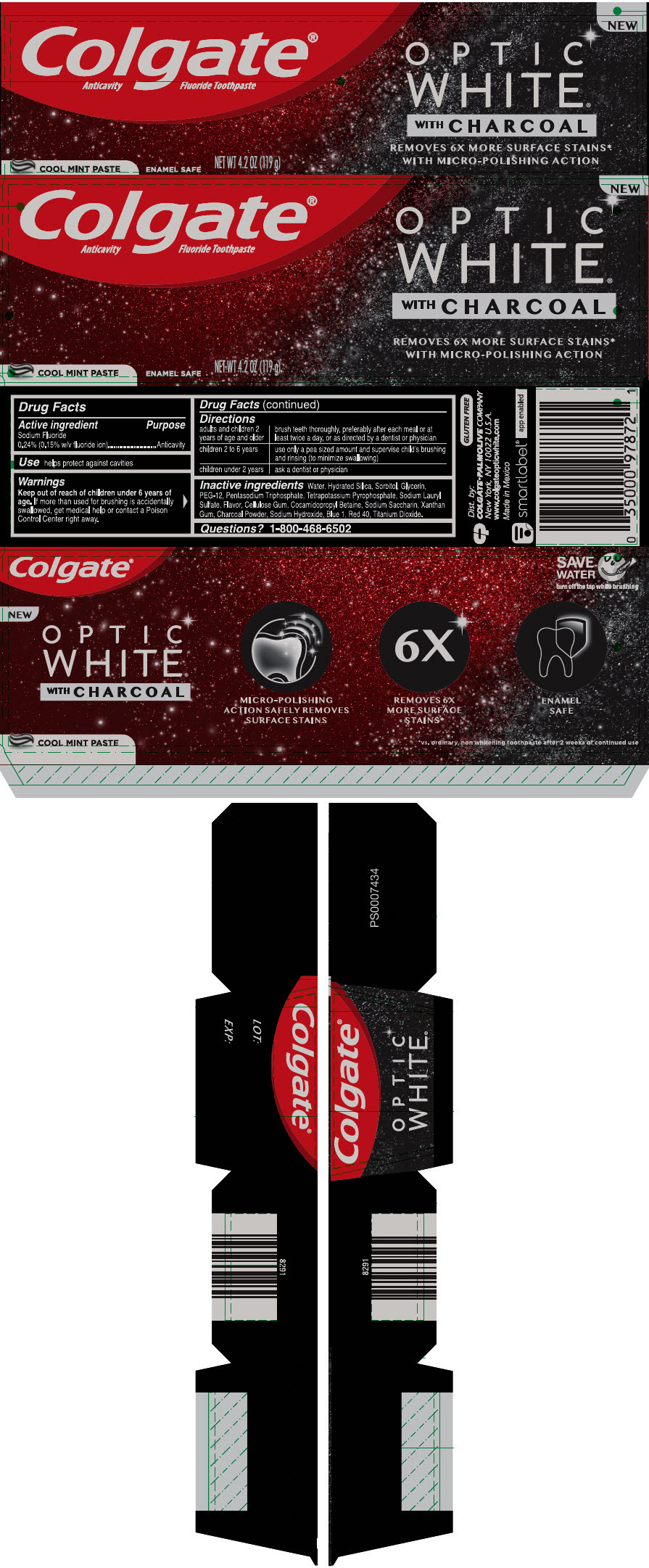 DRUG LABEL: Colgate Optic White Charcoal
NDC: 35000-988 | Form: PASTE, DENTIFRICE
Manufacturer: Colgate-Palmolive Company
Category: otc | Type: HUMAN OTC DRUG LABEL
Date: 20191209

ACTIVE INGREDIENTS: SODIUM FLUORIDE 1.1 mg/1 g
INACTIVE INGREDIENTS: WATER 191.18 mg/1 g; HYDRATED SILICA; SORBITOL; GLYCERIN; POLYETHYLENE GLYCOL 600; SODIUM TRIPOLYPHOSPHATE ANHYDROUS; POTASSIUM PYROPHOSPHATE; SODIUM LAURYL SULFATE; CARBOXYMETHYLCELLULOSE SODIUM, UNSPECIFIED; COCAMIDOPROPYL BETAINE; SACCHARIN SODIUM; XANTHAN GUM; SODIUM HYDROXIDE; ACTIVATED CHARCOAL; FD&C BLUE NO. 1; FD&C RED NO. 40; TITANIUM DIOXIDE

Colgate® Optic White® Charcoal

Drug Facts

Active ingredient

Sodium Fluoride
0.24% (0.15% w/v fluoride ion)

Purpose

Anticavity

Use

helps protect against cavities

Warnings

Keep out of reach of children under 6 years of age. If more than used for brushing is accidentally swallowed, get medical help or contact a Poison Control Center right away.

Directions

adults and children 2 years of age and older | brush teeth thoroughly, preferably after each meal or at least twice a day, or as directed by a dentist or physician
children 2 to 6 years | use only a pea sized amount and supervise child's brushing and rinsing (to minimize swallowing)
children under 2 years | ask a dentist or physician

Inactive ingredients

Water, Hydrated Silica, Sorbitol, Glycerin, PEG-12, Pentasodium Triphosphate, Tetrapotassium Pyrophosphate, Sodium Lauryl Sulfate, Flavor, Cellulose Gum, Cocamidopropyl Betaine, Sodium Saccharin, Xanthan Gum, Charcoal Powder, Sodium Hydroxide, Blue 1, Red 40, Titanium Dioxide.

Questions?

1-800-468-6502

Dist. by:
COLGATE-PALMOLIVE COMPANY
New York, NY 10022 U.S.A.

PRINCIPAL DISPLAY PANEL - 119 g Tube Carton

NEW

Colgate®
Anticavity Fluoride Toothpaste

OPTIC
WHITE®
WITH CHARCOAL

REMOVES 6X MORE SURFACE STAINS*
WITH MICRO-POLISHING ACTION

COOL MINT PASTE
ENAMEL SAFE
NET WT 4.2 OZ (119 g)